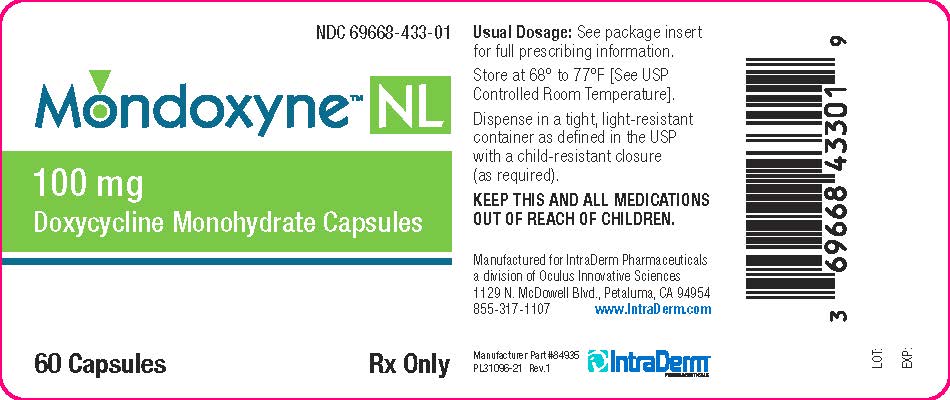 DRUG LABEL: Mondoxyne NL 100mg
NDC: 69668-433 | Form: CAPSULE
Manufacturer: Oculus Innovative Sciences
Category: prescription | Type: HUMAN PRESCRIPTION DRUG LABEL
Date: 20150911

ACTIVE INGREDIENTS: DOXYCYCLINE 100 mg/100 mg

Monodoxyne NL 100mg

Warnings Mondoxyne NL 100mg

Keep this and all medications out of the reach of children.